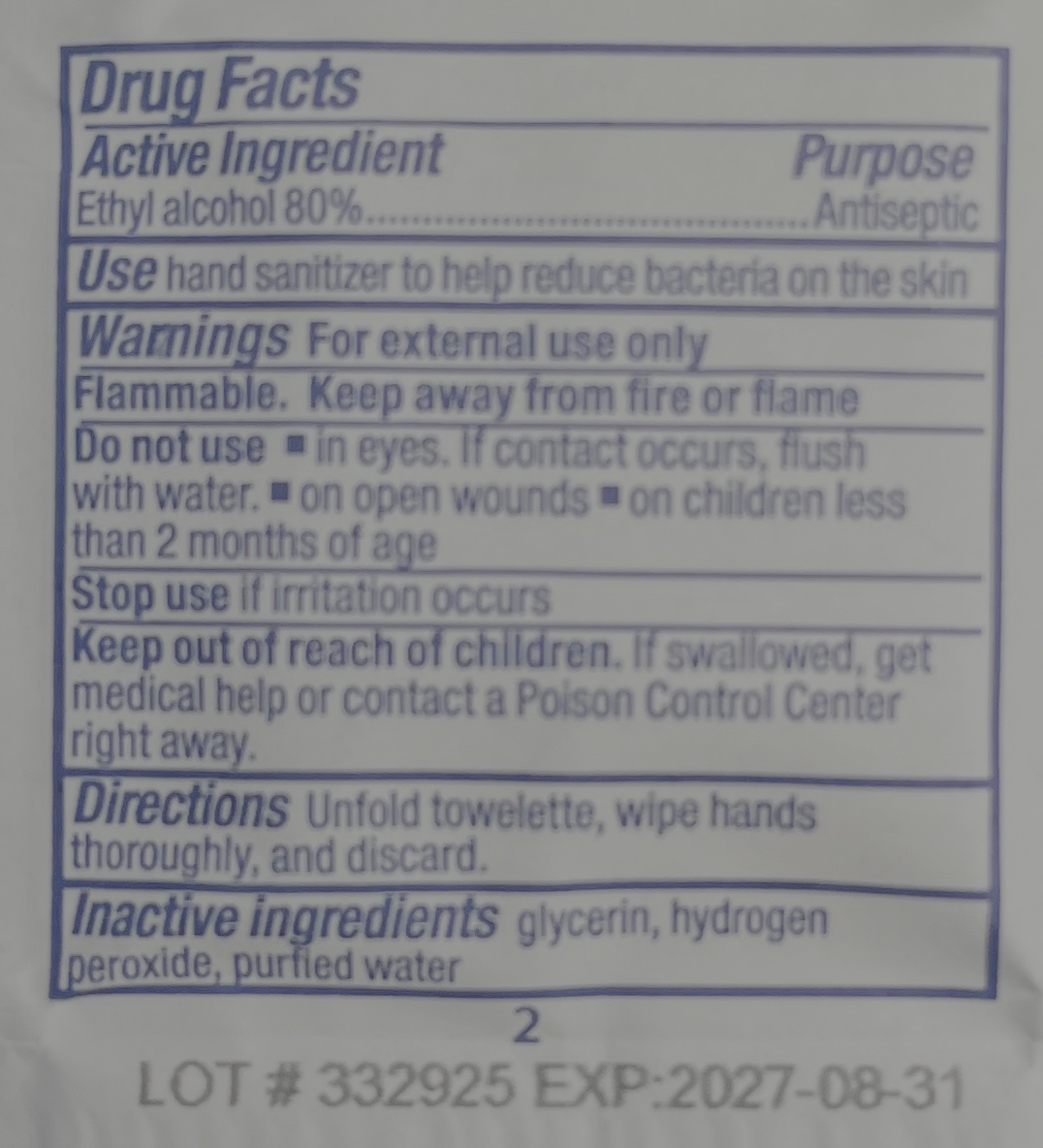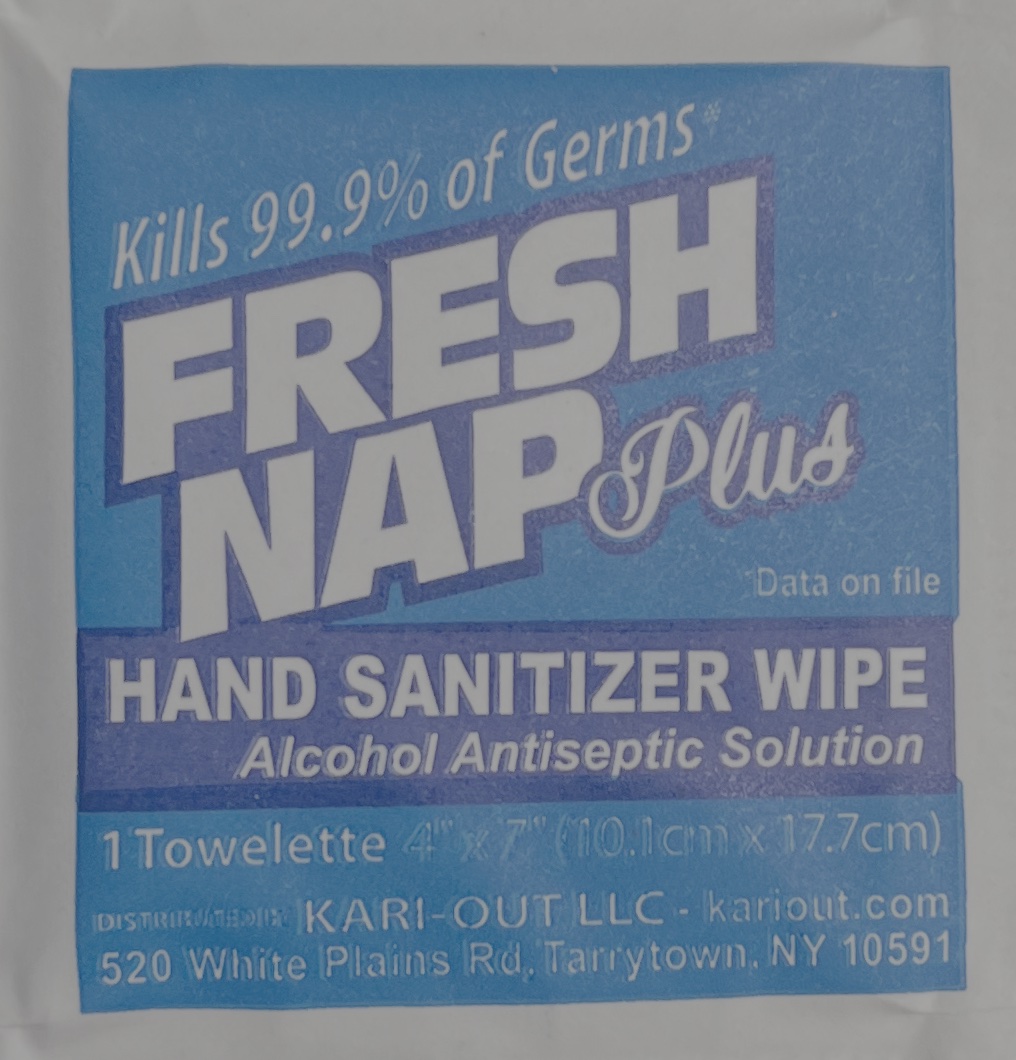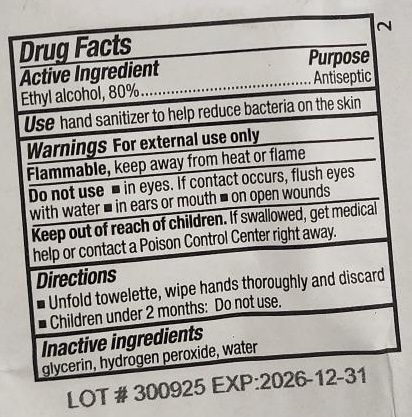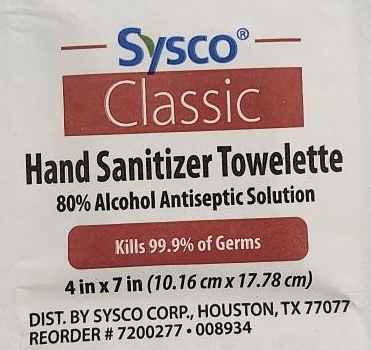 DRUG LABEL: Freshnap Plus - 80% Ethyl Alcohol Towelette
NDC: 79985-200 | Form: CLOTH
Manufacturer: KARI-OUT LLC
Category: otc | Type: HUMAN OTC DRUG LABEL
Date: 20251227

ACTIVE INGREDIENTS: ALCOHOL 80 mL/100 mL
INACTIVE INGREDIENTS: WATER; GLYCERIN; HYDROGEN PEROXIDE

Freshnap Plus - 80% Alcohol Towelette

Active Ingredient

Purpose

Antiseptic

Uses

- hand sanitizer to help reduce bacteria on the skin.

Warnings

For external use only.

Fammable.

Keep away from fire or flame

Do Not Use

- in eyes. If contact occurs, flush with water.
- on open wounds
- on children less than 2 months of age

Stop using and ask a doctor if

Stop use if irritation occurs

Keep out of reach of children

- If swallowed, get medical help or contact a Poison Control Center right away.

Directions

- Unfold towelette, wipe hands thoroughly and discard.

Inactive ingredients

Glycerin, Hydrogen Peroxide, Purfied Water

Package Labeling:

Fresh Nap Plus (Kari-Out) - Package Back

Hand Sanitizer Towelette (Packaged for Sysco) - Package Back

Hand Sanitizer Towelette (Packaged for Sysco) - Package Front

Fresh Nap Plus (Kari-Out) - Package Front